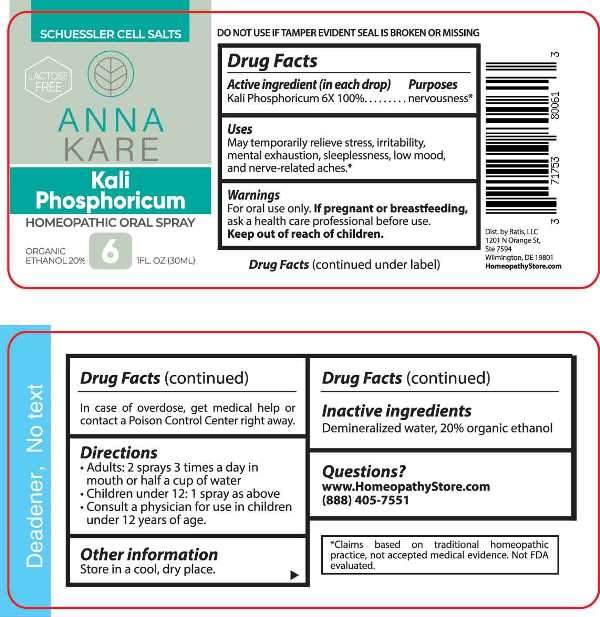 DRUG LABEL: Kali Phosphoricum
NDC: 71753-8006 | Form: SPRAY
Manufacturer: Ratis, LLC
Category: homeopathic | Type: HUMAN OTC DRUG LABEL
Date: 20230525

ACTIVE INGREDIENTS: DIBASIC POTASSIUM PHOSPHATE 6 [hp_X]/1 mL
INACTIVE INGREDIENTS: WATER; ALCOHOL

DRUG FACTS:

ACTIVE INGREDIENT:

(in each drop) Kali Phosphoricum 6X 100%.

PURPOSE:

Kali Phosphoricum - nervousness*

USES:

May temporarily relieve stress, irritability, mental exhaustion, sleeplessness, low mood, and nerve-related aches.*

*Claims based on traditional homeopathic practice, not accepted medical evidence. Not FDA evaluated.

WARNINGS:

For oral use only.

If pregnant or breast-feeding, ask a health care professional before use.

Keep out of reach of children. In case of overdose, get medical help or contact a Poison Control Center right away.

DO NOT USE IF TAMPER EVIDENT SEAL IS BROKEN OR MISSING

KEEP OUT OF REACH OF CHILDREN:

In case of overdose, get medical help or contact a Poison Control Center right away.

DIRECTIONS:

• Adults: 2 sprays 3 times a day in mouth or half a cup of water

• Children under 12: 1 spray as above

• Consult a physician for use in children under 12 years of age.

Store in a cool, dry place.

INACTIVE INGREDIENTS:

Demineralized water, 20% organic ethanol

QUESTIONS:

Dist. by Ratis, LLC

1201 N Orange St,

Ste 7594

Wilmington, DE 19801

www.HomeopathyStore.com

(888) 405-7551

PACKAGE LABEL DISPLAY:

SCHUESSLER CELL SALTS

LACTOSE FREE

ANNA

KARE

Kali

Phosphoricum

HOMEOPATHIC ORAL SPRAY

1 FL. OZ (30ML)